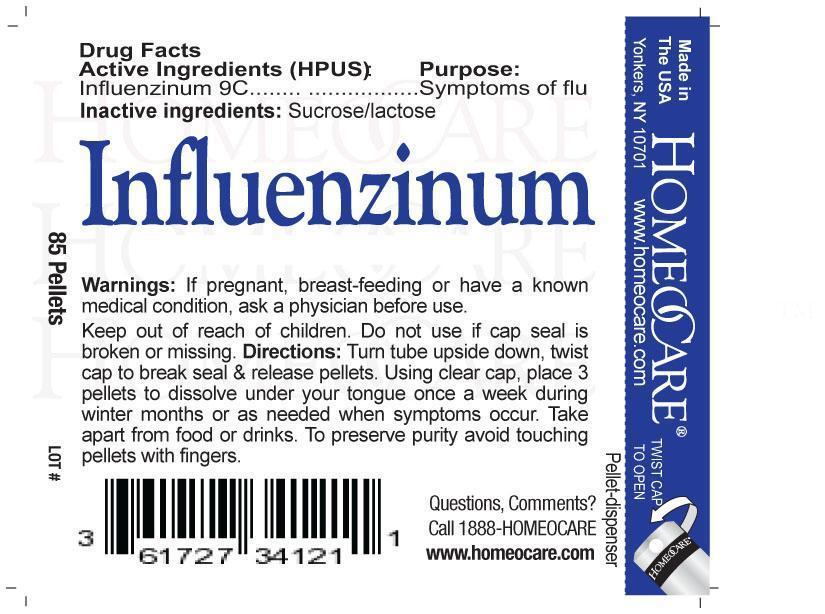 DRUG LABEL: Influenzinum
NDC: 61727-341 | Form: PELLET
Manufacturer: Homeocare Laboratories
Category: homeopathic | Type: HUMAN OTC DRUG LABEL
Date: 20181231

ACTIVE INGREDIENTS: INFLUENZA A VIRUS 9 [hp_C]/4 g; INFLUENZA B VIRUS 9 [hp_C]/4 g
INACTIVE INGREDIENTS: SUCROSE; LACTOSE

Influenzinum

Active Ingredients:

Influenzinum 9C

Inactive Ingredients:

Sucrose, lactose.

Purpose:

Symptoms of flu.

Keep out of reach of children.

Indications & Usage:

Turn tube upside down, twist cap to break seal & release pellets. Using clear cap, place 3 pellets to dissolve under your tongue once a week during winter months or as needed when symptoms occur. Take apart from food or drinks. To preserve purity avoid touching pellets with fingers.

Warnings:

If pregnant, breast feeding or have a known medical condition, ask a physician before use.

Dosage & Administration:

Turn tube upside down, twist cap to break seal & release pellets. Using clear cap, place 3 pellets to dissolve under your tongue once a week during winter months or as needed when symptoms occur. Take apart from food or drinks. To preserve purity avoid touching pellets with fingers.